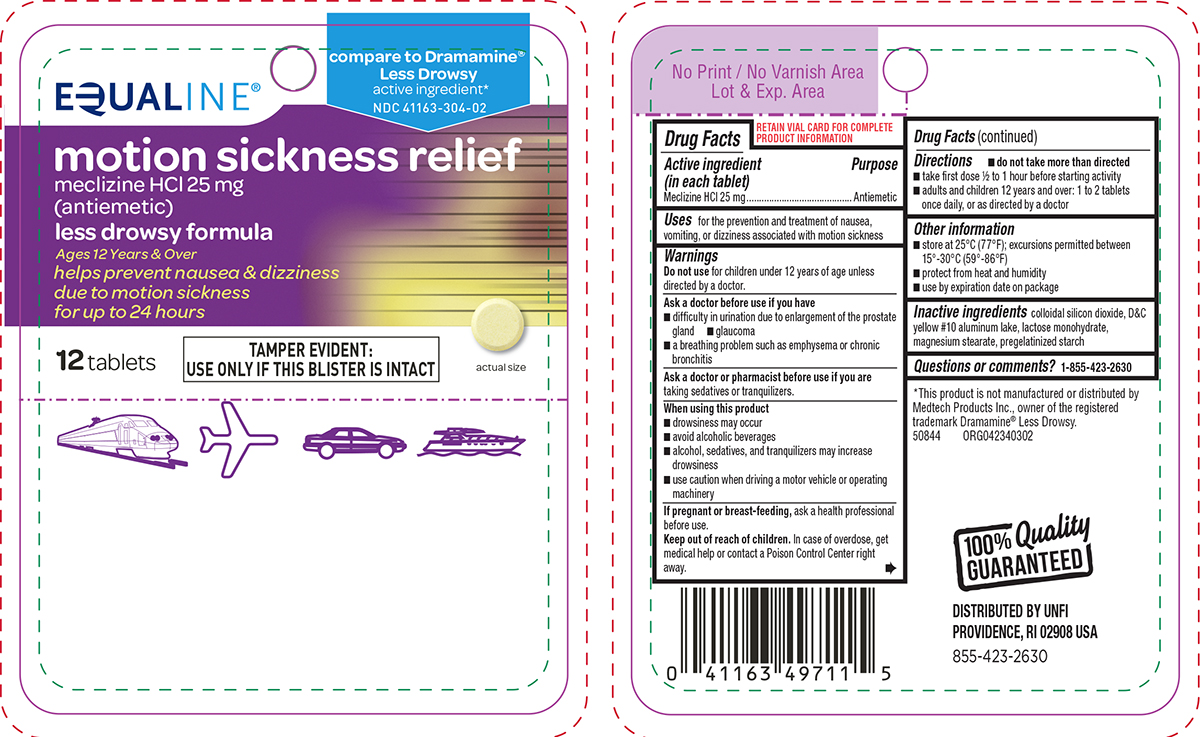 DRUG LABEL: Motion Sickness Relief
NDC: 41163-304 | Form: TABLET
Manufacturer: United Natural Foods, Inc. dba UNFI
Category: otc | Type: HUMAN OTC DRUG LABEL
Date: 20260112

ACTIVE INGREDIENTS: MECLIZINE HYDROCHLORIDE 25 mg/1 1
INACTIVE INGREDIENTS: SILICON DIOXIDE; D&C YELLOW NO. 10 ALUMINUM LAKE; LACTOSE MONOHYDRATE; MAGNESIUM STEARATE; STARCH, CORN

Equaline 44-403

Active ingredient (in each tablet)

Meclizine HCl 25 mg

Purpose

Antiemetic

Uses

for the prevention and treatment of nausea, vomiting, or dizziness associated with motion sickness

Warnings

Do not use

for children under 12 years of age unless directed by a doctor.

Ask a doctor before use if you have

- glaucoma
- difficulty in urination due to enlargement of the prostate gland
- a breathing problem such as emphysema or chronic bronchitis

Ask a doctor or pharmacist before use if you are

taking sedatives or tranquilizers.

When using this product

- drowsiness may occur
- avoid alcoholic beverages
- alcohol, sedatives, and tranquilizers may increase drowsiness
- use caution when driving a motor vehicle or operating machinery

If pregnant or breast-feeding,

ask a health professional before use.

Keep out of reach of children.

In case of overdose, get medical help or contact a Poison Control Center right away.

Directions

- do not take more than directed
- take first dose 1/2 to 1 hour before starting activity
- adults and children 12 years and over: 1 to 2 tablets once daily, or as directed by a doctor

Other information

- store at 25ºC (77ºF); excursions permitted between 15º-30ºC (59º-86ºF)
- protect from heat and humidity
- use by expiration date on package

Inactive ingredients

colloidal silicon dioxide, D&C yellow #10 aluminum lake, lactose monohydrate, magnesium stearate, pregelatinized starch

Questions or comments?

1-855-423-2630

Principal Display Panel

EQUALINE®

compare to Dramamine®
Less Drowsy
active ingredient*
NDC 41163-304-02

motion sickness relief
meclizine HCl 25 mg
(antiemetic)

less drowsy formula

Ages 12 Years & Over
helps prevent nausea & dizziness
due to motion sickness
for up to 24 hours

12 tablets

TAMPER EVIDENT:
USE ONLY IF THIS BLISTER IS INTACT

actual size

*This product is not manufactured or distributed by
Medtech Products Inc., owner of the registered
trademark Dramamine® Less Drowsy.
50844 ORG042340302

100% Quality
GUARANTEED

DISTRIBUTED BY UNFI
PROVIDENCE, RI 02908 USA
855-423-2630

Equaline 44-403